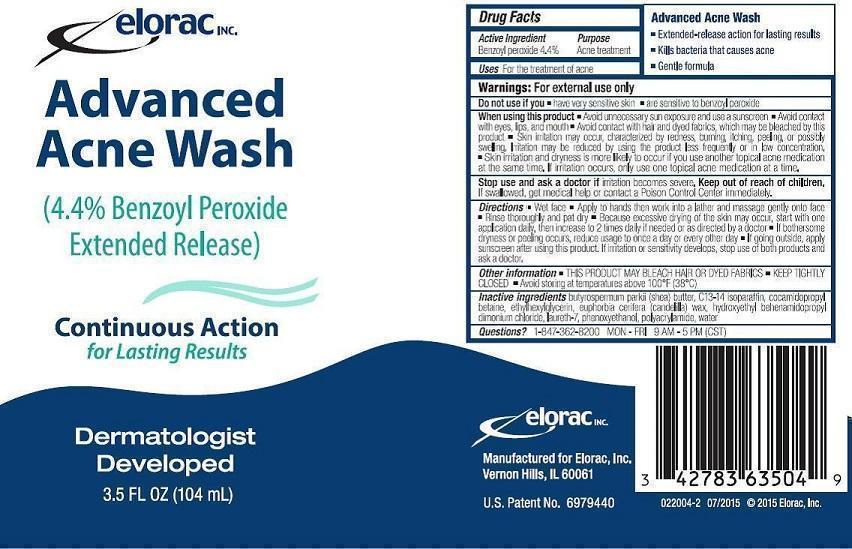 DRUG LABEL: Advanced Acne Wash
NDC: 42783-635 | Form: LIQUID, EXTENDED RELEASE
Manufacturer: Elorac, Inc.
Category: otc | Type: HUMAN OTC DRUG LABEL
Date: 20151008

ACTIVE INGREDIENTS: BENZOYL PEROXIDE 44 mg/1 mL
INACTIVE INGREDIENTS: SHEA BUTTER; C13-14 ISOPARAFFIN; COCAMIDOPROPYL BETAINE; ETHYLHEXYLGLYCERIN; CANDELILLA WAX; HYDROXYETHYL BEHENAMIDOPROPYL DIMONIUM CHLORIDE; LAURETH-7; PHENOXYETHANOL; WATER

Advanced Acne Wash (4.4% benzoyl peroxide extended release)

Continous Action for Lasting Results

4.4% Benzoyl Peroxide

Dermatologist Developed

Drug Facts

Active Ingredient

Benzoyl peroxide 4.4%

Purpose

Acne treatment

Uses

For the treatment of acne

Warnings

For external use only

Do not use if you

have very sensitive skin

are sensitive to benzoyl peroxide

When using this product

Avoid unnecessary sun exposure and use a sunscreen

Avoid contact with eyes, lips, and mouth

Avoid contact with hair and dyed fabrics, which may be bleached by this product

Skin irritation may occur, characterized by redness, burning, itching, peeling, or possibly swelling. Irritation may be reduced by using the product less frequently.

Skin irritation and dryness is more likely to occur if you use another topical acne medication at the same time. If irritation occurs, only use one topical acne medication at a time.

Stop use and ask a doctor if

irritation becomes severe

Keep out of reach of children

If swallowed, get medical help or contact a Poison Control Center immediately.

Directions

Wet face

Apply to hands then work into a lather and massage gently onto face

Rinse thoroughly and pat dry

Because excessive drying of the skin may occur, start with one application daily, then increase to 2 times daily if needed or as directed by a doctor

If bothersome dryness or peeling occurs, reduce usage to once a day or every other day

If going outside, apply sunscreen after using this product.

If irritation or sensitivity develops, stop use of both products and ask a doctor.

Other information

THIS PRODUCT MAY BLEACH HAIR OR DYED FABRICS

KEEP TIGHTLY CLOSED

Avoid storing at temperatures above 100°F (38°C)

Inactive ingredients

Butyrospermum Parkii (Shea) Butter, C13-14 Isoparaffin, Cocamidopropyl Betaine, Ethylhexylglycerin, Euphorbia Cerifera (Candelilla) Wax, Hydroxyethyl Behenamidopropyl Dimonium Chloride, Laureth-7, Phenoxyethanol, Polyacrylamide, Water

Questions?

1-847-362-8200 MON - FRI 9 AM - 5 PM (CST)

Advanced Acne Wash

Extended - release action for lasting results

Kills bacteria that cause acne

Gentle formula

Manufactured for Elorac, Inc.

Vernon Hills, IL 60061

U.S. Patent No. 6979440

022004 - 2 07/2015 ©2015 Elorac, Inc.

PACKAGE LABEL

NDC 42783-635-04

Elorac, Inc.

Advanced Acne Wash